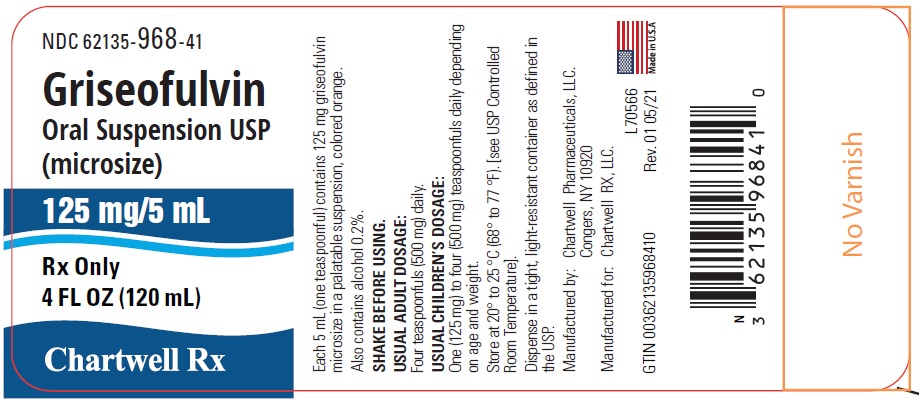 DRUG LABEL: Griseofulvin
NDC: 62135-968 | Form: SUSPENSION
Manufacturer: Chartwell RX, LLC.
Category: prescription | Type: HUMAN PRESCRIPTION DRUG LABEL
Date: 20241028

ACTIVE INGREDIENTS: GRISEOFULVIN 125 mg/5 mL
INACTIVE INGREDIENTS: ALCOHOL; DOCUSATE SODIUM; FD&C RED NO. 40; FD&C YELLOW NO. 6; MAGNESIUM ALUMINUM SILICATE; MENTHOL, UNSPECIFIED FORM; METHYLPARABEN; PROPYLENE GLYCOL; PROPYLPARABEN; WATER; SACCHARIN SODIUM; SODIUM ALGINATE; SUCROSE

Griseofulvin Oral Suspension, USP (microsize)
125 mg/5 mL
Rx Only

Description

Griseofulvin is an antibiotic derived from a species of Penicillium. Each 5 mL of Griseofulvin Oral Suspension, USP contains 125 mg of griseofulvin (microsize) and also contains alcohol (0.2%), docusate sodium, FD&C Red No. 40, FD&C Yellow No. 6, magnesium aluminum silicate, menthol, methylparaben, orange cream flavors, propylene glycol, propylparaben, purified water, saccharin sodium, simethicone emulsion, sodium alginate and sucrose.

Clinical Pharmacology

Griseofulvin Oral Suspension, USP acts systemically to inhibit the growth of Trichophyton, Microsporum, and Epidermophyton genera of fungi. Fungistatic amounts are deposited in the keratin, which is gradually exfoliated and replaced by noninfected tissue.

Griseofulvin absorption from the gastrointestinal tract varies considerably among individuals, mainly because of insolubility of the drug in aqueous media of the upper G.I. tract. The peak serum level found in fasting adults given 0.5 gm occurs at about four hours and ranges between 0.5 and 2.0 mcg/mL.

It should be noted that some individuals are consistently "poor absorbers" and tend to attain lower blood levels at all times. This may explain unsatisfactory therapeutic results in some patients. Better blood levels can probably be attained in most patients if griseofulvin is administered after a meal with a high fat content.

Indications and Usage

Major indications for Griseofulvin Oral Suspension, USP are:

Tinea capitis (ringworm of the scalp)
Tinea corporis (ringworm of the body)
Tinea pedis (athlete's foot)
Tinea unguium (onychomycosis; ringworm of the nails)
Tinea cruris (ringworm of the thigh)
Tinea barbae (barber’s itch)

Griseofulvin Oral Suspension, USP inhibits the growth of those genera of fungi that commonly cause ringworm infections of the hair, skin, and nails, such as:
Trichophyton rubrum
Trichophyton tonsurans
Trichophyton mentagrophytes
Trichophyton interdigitalis
Trichophyton verrucosum
Trichophyton sulphureum
Trichophyton schoenleini
Microsporum audouini
Microsporum canis
Microsporum gypseum
Epidermophyton floccosum
Trichophyton megnini
Trichophyton gallinae
Trichophyton crateriform

Note: Prior to therapy, the type of fungi responsible for the infection should be identified. The use of the drug is not justified in minor or trivial infections which will respond to topical antifungal agents alone.

It is not effective in:
Bacterial infections
Candidiasis (Moniliasis)
Histoplasmosis
Actinomycosis
Sporotrichosis
Chromoblastomycosis
Coccidioidomycosis
North American Blastomycosis
Cryptococcosis (Torulosis)
Tinea versicolor
Nocardiosis

Contraindications

This drug is contraindicated in patients with porphyria, hepatocellular failure, and in individuals with a history of hypersensitivity to griseofulvin.

Two cases of conjoined twins have been reported in patients taking griseofulvin during the first trimester of pregnancy. Griseofulvin should not be prescribed to pregnant patients.

Warnings

Prophylactic Usage: Safety and efficacy of prophylactic use of this drug has not been established.

Chronic feeding of griseofulvin, at levels ranging from 0.5-2.5% of the diet, resulted in the development of liver tumors in several strains of mice, particularly in males. Smaller particle sizes result in an enhanced effect. Lower oral dosage levels have not been tested. Subcutaneous administration of relatively small doses of griseofulvin once a week during the first three weeks of life has also been reported to induce hepatomata in mice. Although studies in other animal species have not yielded evidence of tumorigenicity, these studies were not of adequate design to form a basis for conclusions in this regard.

In subacute toxicity studies, orally administered griseofulvin produced hepatocellular necrosis in mice, but this has not been seen in other species. Disturbances in porphyrin metabolism have been reported in griseofulvin-treated laboratory animals. Griseofulvin has been reported to have a colchicine-like effect on mitosis and cocarcinogenicity with methylcholanthrene in cutaneous tumor induction in laboratory animals.

Reports of animal studies in the Soviet literature state that a griseofulvin preparation was found to be embryotoxic and teratogenic on oral administration to pregnant Wistar rats. Rat reproduction studies done in the United States and Great Britain were inconclusive in this regard. Pups with abnormalities have been reported in the litters of a few bitches treated with griseofulvin. Because the potential for adverse effects on the human fetus cannot be ruled out, additional contraceptive precautions should be taken during treatment with griseofulvin and for a month after termination of treatment. Griseofulvin Oral Suspension, USP should not be prescribed to women intending to become pregnant within one month following cessation of therapy.

Suppression of spermatogenesis has been reported to occur in rats but investigation in man failed to confirm this. Griseofulvin interferes with chromosomal distribution during cell division, causing aneuploidy in plant and mammalian cells. These effects have been demonstrated in vitro at concentrations that may be achieved in the serum with the recommended therapeutic dosage.

Since griseofulvin has demonstrated harmful effects in vitro on the genotype in bacteria, plants, and fungi, males should wait at least six months after completing griseofulvin therapy before fathering a child.

Precautions

Patients on prolonged therapy with any potent medication should be under close observation. Periodic monitoring of organ system function, including renal, hepatic and hemopoietic, should be done.

Since griseofulvin is derived from species of penicillin, the possibility of cross sensitivity with penicillin exists; however, known penicillin-sensitive patients have been treated without difficulty.

Since a photosensitivity reaction is occasionally associated with griseofulvin therapy, patients should be warned to avoid exposure to intense natural or artificial sunlight. Should a photosensitivity reaction occur, lupus erythematosus may be aggravated.

Drug Interactions: Patients on warfarin-type anticoagulant therapy may require dosage adjustment of the anticoagulant during and after griseofulvin therapy. Concomitant use of barbiturates usually depresses griseofulvin activity and may necessitate raising the dosage.

The concomitant administration of griseofulvin has been reported to reduce the efficacy of oral contraceptives and to increase the incidence of breakthrough bleeding.

Adverse Reactions

When adverse reactions occur, they are most commonly of the hypersensitivity type such as skin rashes, urticaria and rarely, angioneurotic edema or erythema multiforme-like drug reaction, and may necessitate withdrawal of therapy and appropriate countermeasures. Paresthesias of the hands and feet have been reported rarely after extended therapy. Other side effects reported occasionally are oral thrush, nausea, vomiting, epigastric distress, diarrhea, headache, fatigue, dizziness, insomnia, mental confusion and impairment of performance of routine activities.

Proteinuria and leukopenia have been reported rarely. Administration of the drug should be discontinued if granulocytopenia occurs.

When rare, serious reactions occur with griseofulvin, they are usually associated with high dosages, long periods of therapy, or both.

Dosage and Administration

Accurate diagnosis of the infecting organism is essential. Identification should be made either by direct microscopic examination of a mounting of infected tissue in a solution of potassium hydroxide or by culture on an appropriate medium.

Medication must be continued until the infecting organism is completely eradicated as indicated by appropriate clinical or laboratory examination. Representative treatment periods are tinea capitis, 4 to 6 weeks; tinea corporis, 2 to 4 weeks; tinea pedis, 4 to 8 weeks; tinea unguium – depending on rate of growth – fingernails, at least 4 months; toenails, at least 6 months.

General measures in regard to hygiene should be observed to control sources of infection or reinfection. Concomitant use of appropriate topical agents is usually required, particularly in treatment of tinea pedis since in some forms of athlete's foot, yeasts and bacteria may be involved. Griseofulvin will not eradicate the bacterial or monilial infection.

Adults: A daily dose of 500 mg will give a satisfactory response in most patients with tinea corporis, tinea cruris, and tinea capitis.

For those fungus infections more difficult to eradicate such as tinea pedis and tinea unguium, a daily dose of 1 gram is recommended.

Children: Approximately 5 mg per pound of body weight per day is an effective dose for most children. On this basis the following dosage schedule for children is suggested:
Children weighing 30 to 50 pounds - 125 mg to 250 mg daily.
Children weighing over 50 pounds - 250 mg to 500 mg daily.

How Supplied

Griseofulvin Oral Suspension, USP (microsize) 125 mg per 5 mL is available as follows:
4 fl oz (120 mL) bottle (NDC 62135-968-41)

Dispense Griseofulvin Oral Suspension, USP in a tight, light-resistant container as defined in the USP.

STORAGE

Store at 20° to 25°C (68° to 77°F) [see USP Controlled Room Temperature].

Manufactured by:
Chartwell Pharmaceuticals, LLC.
Congers, NY 10920

Manufactured for:
Chartwell RX, LLC.
Congers, NY 10920
L70567 Rev: 08/2021

PRINCIPAL DISPLAY PANEL

Griseofulvin Oral Suspension, USP (microsize) 125 mg/5 mL - NDC 62135-968-41 - Label